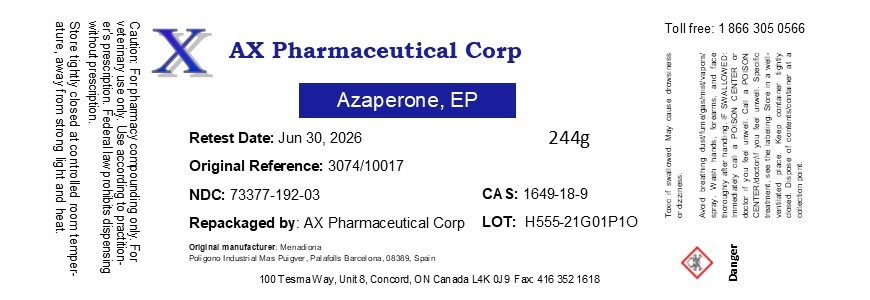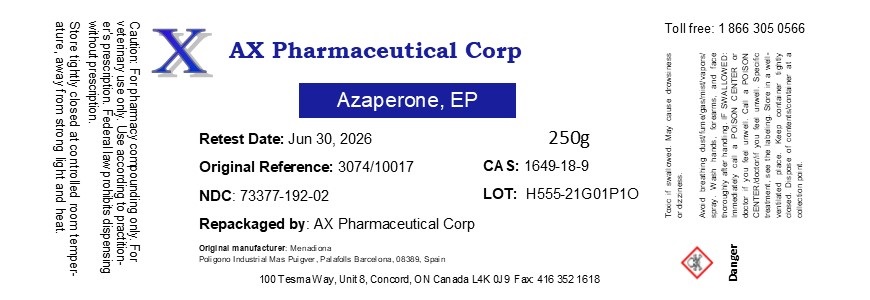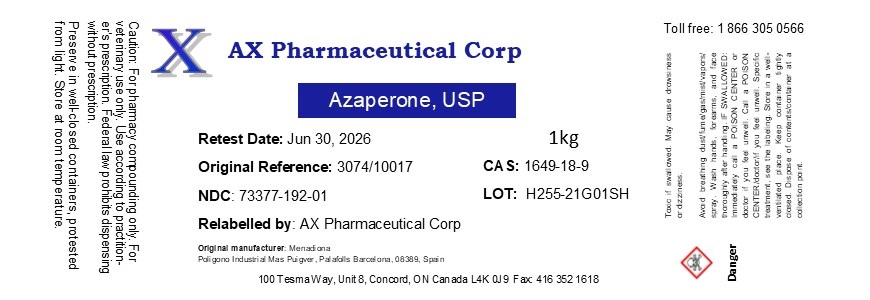 DRUG LABEL: Azaperone
NDC: 73377-192 | Form: POWDER
Manufacturer: AX Pharmaceutical Corp
Category: other | Type: BULK INGREDIENT - ANIMAL DRUG
Date: 20230327

ACTIVE INGREDIENTS: AZAPERONE 1 g/1 g

Azaperone